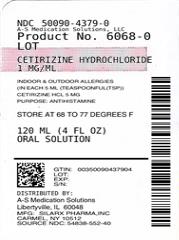 DRUG LABEL: Cetirizine Hydrochloride
NDC: 50090-4379 | Form: SOLUTION
Manufacturer: A-S Medication Solutions
Category: otc | Type: HUMAN OTC DRUG LABEL
Date: 20210416

ACTIVE INGREDIENTS: CETIRIZINE HYDROCHLORIDE 5 mg/5 mL
INACTIVE INGREDIENTS: CALCIUM ACETATE; ACETIC ACID; GLYCERIN; METHYLPARABEN; PROPYLENE GLYCOL; PROPYLPARABEN; WATER

Cetirizine Hydrochloride Oral Solution - Allergy

Drug Facts

Active ingredient (in each 5 mL (teaspoonful(tsp)): Cetirizine HCl 5 mg

Purpose: Antihistamine

Uses

temporarily relieves these symptoms due to hay fever or other upper respiratory allergies:

- runny nose
- itchy, watery eyes
- sneezing
- itching of the nose or throat

Warnings

Do not use

if you have ever had an allergic reaction to this product or any of its ingredients or to an antihistamine containing hydroxyzine

Ask a doctor before use if you have

liver or kidney disease. Your doctor should determine if you need a different dose.

Ask a doctor or pharmacist before use if you are

taking tranquilizers or sedatives.

When using this product

- drowsiness may occur
- avoid alcoholic drinks
- alcohol, sedatives, and tranquilizers may increase drowsiness
- be careful when driving a motor vehicle or operating machinery

Stop use and ask a doctor if

an allergic reaction to this product occurs. Seek medical help right away.

If pregnant or breast-feeding

- If breast-feeding: not recommended
- if pregnant: ask a health professional before use.

Keep out of reach of children. In case of overdose, get medical help or contact a Poison Control Center right away.(1-800-222-1222)

Directions

use only with enclosed dosing cup

adults and children 6 years and over | 1 teaspoonful (tsp)(5 mL) or 2 teaspoonfuls (tsp)(10 mL) once daily depending upon severity of symptoms; do not take more than 2 teaspoonfuls (tsp)(10 mL) in 24 hours.
adults 65 years and over | 1 teaspoonful (tsp)(5 mL) once daily; do not take more than 1 teaspoonful (tsp)(5 mL) in 24 hours.
children 2 to under 6 years of age | 1/2 teaspoonful (tsp)(2.5 mL) once daily. If needed, dose can be increased to a maximum of 1 teaspoonful (tsp)(5 mL) once daily or 1/2 teaspoonful (tsp)(2.5 mL) every 12 hours. Do not give more than 1 teaspoonful (tsp)(5 mL) in 24 hours.
children under 2 years of age | ask a doctor
consumers with liver or kidney disease | ask a doctor

Other information
Store between 20º to 25ºC (68º to 77ºF)

Inactive ingredients

calcium acetate, grape flavor, glacial acetic acid, glycerin, methylparaben, propylene glycol, propylparaben, purified water.

Questions?

Call 1-844-834-0530

Drug Facts

Active ingredient (in each 5 mL (teaspoonful)): Cetirizine HCl 5 mg

Purpose: Antihistamine

Uses

relieves itching due to hives (urticaria). This product will not prevent hives or an allergic skin reaction from occurring.

Warnings

Severe Allergy Warning: Get emergency help immediately if you have hives along with any of the following symptoms:

- trouble swallowing
- dizziness or loss of consciousness
- swelling of tongue
- swelling in or around mouth
- trouble speaking
- drooling
- wheezing or problems breathing

These symptoms may be signs of anaphylactic shock. This condition can be life threatening if not treated by health professional immediately. Symptoms of anaphylactic shock may occur when hives first appear or up to a few hours later.
Not a Substitute for Epinephrine. If your doctor has prescribed an epinephrine injector for “anaphylaxis” or severe allergy symptoms that could occur with your hives, never use this product as a substitute for the epinephrine injector. If you have been prescribed an epinephrine injector, you should carry it with you at all times.

Do not use

- to prevent hives from any known cause such as:
- foods
- insect stings
- medicines
- latex or rubber gloves because this product will not stop hives from occurring. Avoiding the cause of your hives is the only way to prevent them. Hives can sometimes be serious. If you do not know the cause of your hives, see your doctor for a medical exam. Your doctor may be able to help you find a cause.
- if you have ever had an allergic reaction to this product or any of its ingredients or to an antihistamine containing hydroxyzine.

Ask a doctor before use if you have

- liver or kidney disease. Your doctor should determine if you need a different dose
- hives that are an unusual color, look bruised or blistered
- hives that do not itch

Ask a doctor or pharmacist before use if you are

taking tranquilizers or sedatives

When using this product

- drowsiness may occur
- avoid alcoholic drinks
- alcohol, sedatives, and tranquilizers may increase drowsiness
- be careful when driving a motor vehicle or operating machinery

Stop use and ask a doctor if

- an allergic reaction to this product occurs. Seek medical help right away.
- symptoms do not improve after 3 days of treatment
- the hives have lasted more than 6 weeks

If pregnant or breast-feeding

- If breast-feeding: not recommended
- if pregnant: ask a health professional before use.

Keep out of reach of children. In case of overdose, get medical help or contact a Poison Control Center right away.

Directions

use only with enclosed dosing cup

adults and children 6 years and over | 1 teaspoonful (5 mL) or 2 teaspoonfuls (10 mL) once daily depending upon severity of symptoms; do not take more than 2 teaspoonfuls (10 mL) in 24 hours
adults 65 years and over | 1 teaspoonful (5 mL) once daily; do not take more than 1 teaspoonful (5 mL) in 24 hours
children under 6 years of age | ask a doctor
consumers with liver or kidney disease | ask a doctor

Other information
Store between 20º to 25ºC (68º to 77ºF)

Inactive ingredients

calcium acetate, grape flavor, glacial acetic acid, glycerin, methylparaben, propylene glycol, propylparaben, purified water

Questions?

Call 1-888-974-5279

Dosing Cup Included

Dosing cup should be washed and left to air dry after each use.

Do not use if carton is open; or if safety seal printed with “SEALED FOR YOUR PROTECTION” around cap of the bottle is broken or missing.

SAVE THIS CARTON FOR FULL LABELING INFORMATION